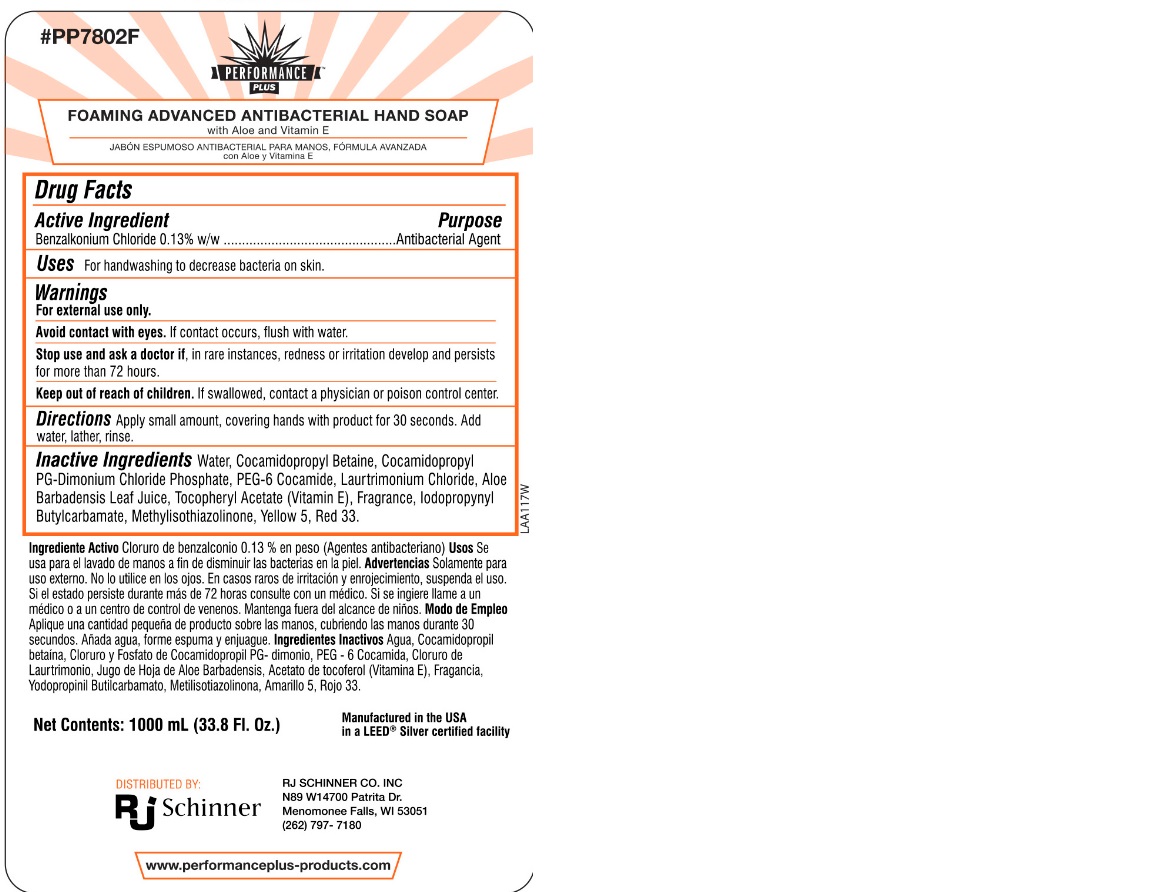 DRUG LABEL: Foaming Antibacterial Hand Wash
NDC: 71303-213 | Form: SOAP
Manufacturer: RJ Schinner
Category: otc | Type: HUMAN OTC DRUG LABEL
Date: 20241218

ACTIVE INGREDIENTS: BENZALKONIUM CHLORIDE 0.013 mg/1 mL
INACTIVE INGREDIENTS: COCAMIDOPROPYL BETAINE; WATER; D&C RED NO. 33; .ALPHA.-TOCOPHEROL ACETATE; IODOPROPYNYL BUTYLCARBAMATE; METHYLISOTHIAZOLINONE; LAURTRIMONIUM CHLORIDE; ALOE VERA LEAF; COCAMIDOPROPYL PG-DIMONIUM CHLORIDE PHOSPHATE; PEG-6 COCAMIDE; HC YELLOW NO. 5

RJ Schninner F213F

Dosage and Administration

Directions Apply small amount, covering hands with product for 30 seconds. Add water, lather, rinse.

Inactive Ingredients

Inactive Ingredients Water, Cocamidopopyl Betaine, Cocamidoprpyl PG-Dimonium Chloride Phosphate, PEG-6 Cocamide, Laurtrimonium Chloride, Aloe Barbadensis Leaf Juice, Tocopheryl Acetate, Fragrance, Iodopropynyl Butylcarbamate, Methylisothiazolinone, Yellow 5, Red 33.

Indications and Uses

Uses For handwashing to decrease bacteria on the skin.

Keep out of reach of children. If swallowed, contact a physician or poison control center.

Purpose Section

Purpose Antibacterial Agent

Active Ingredient Section

Active Ingredient Benzalkonium Chloride 0.13% w/w

Warnings Section

Warnings

For external use only

Avoid contact with eyes. If contact occurs, flush with water.

Stop use and ask a doctor if, in rare instances, redness or irritation develops and persists for more than 72 hours